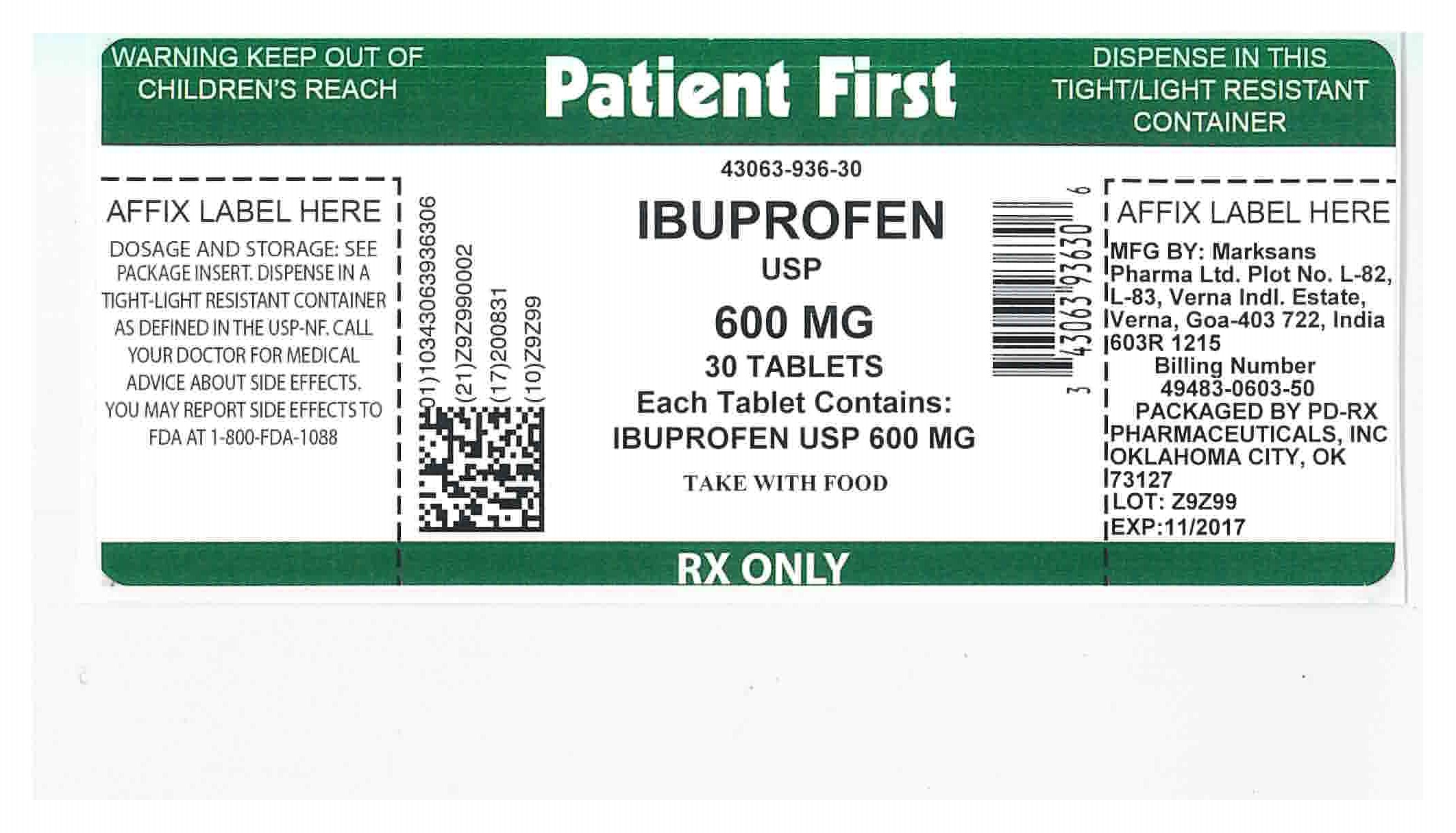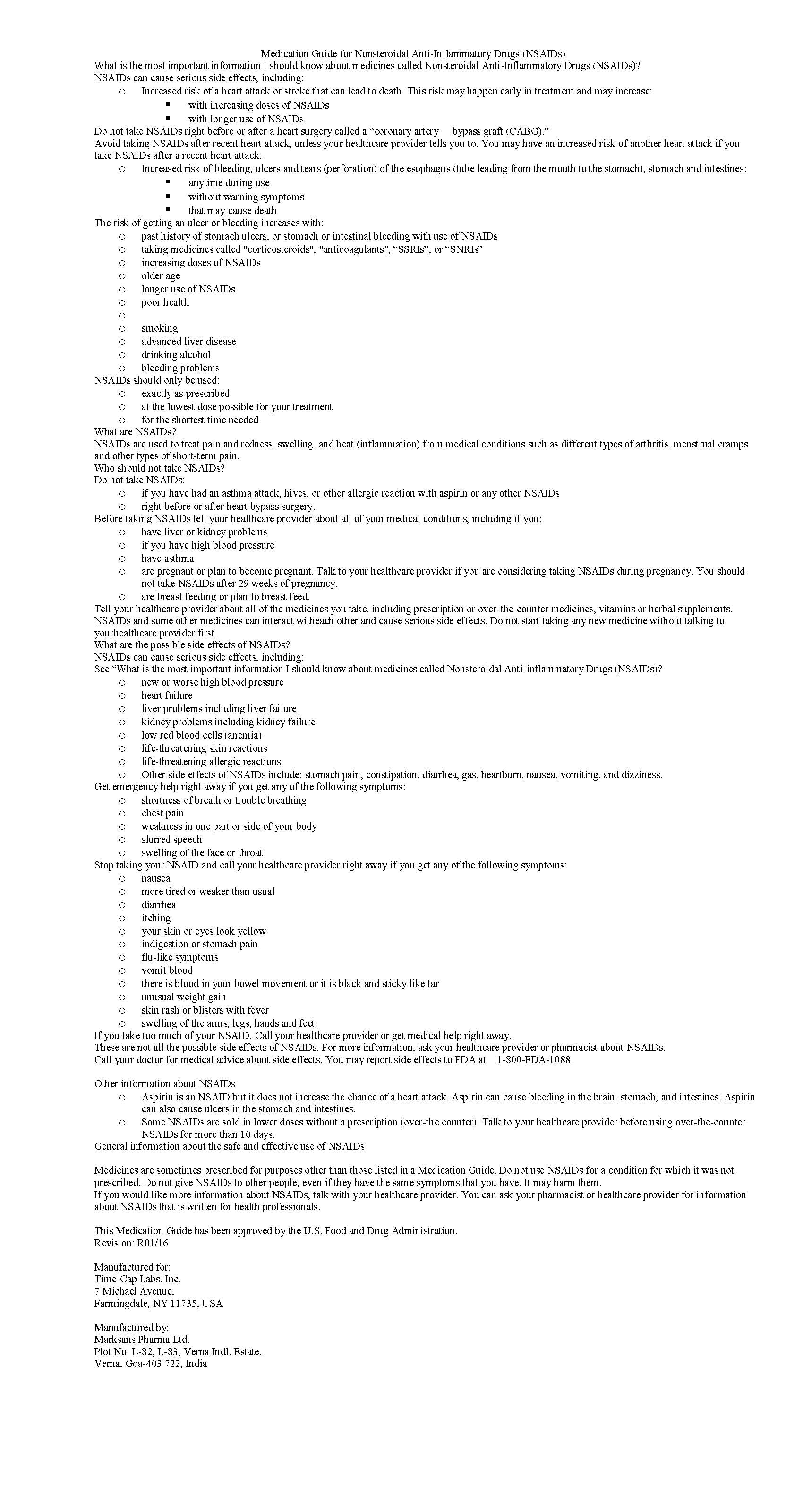 DRUG LABEL: IBUPROFEN
NDC: 43063-936 | Form: TABLET, FILM COATED
Manufacturer: PD-Rx Pharmaceuticals, Inc.
Category: prescription | Type: HUMAN PRESCRIPTION DRUG LABEL
Date: 20230929

ACTIVE INGREDIENTS: IBUPROFEN 600 mg/1 1
INACTIVE INGREDIENTS: SILICON DIOXIDE; CROSCARMELLOSE SODIUM; MAGNESIUM STEARATE; CELLULOSE, MICROCRYSTALLINE; POLYETHYLENE GLYCOL, UNSPECIFIED; POLYVINYL ALCOHOL; STARCH, PREGELATINIZED CORN; TALC; TITANIUM DIOXIDE

IBUPROFEN 600 MG TABLETS

HOW SUPPLIED

600mg (white to off white, capsule shaped, biconvex, film coated tablets debossed with '122' on one side and plain on the other side) Bottles of 30 NDC 43063-936-30